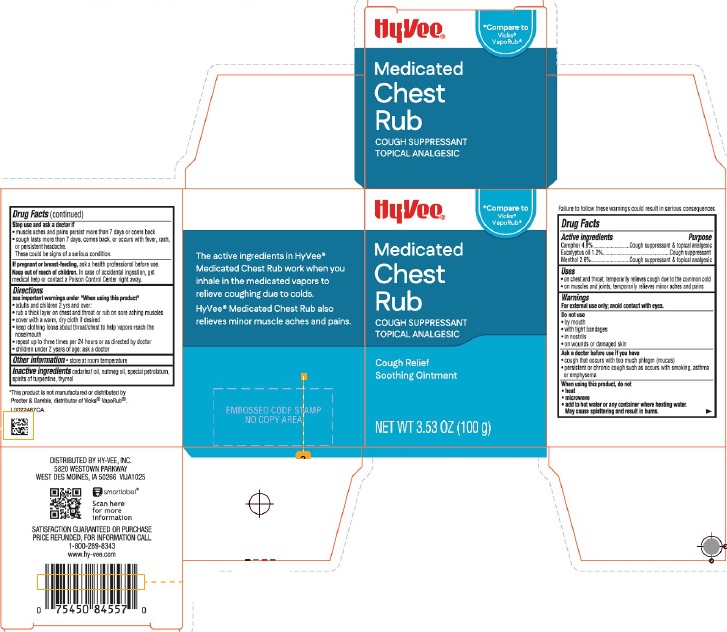 DRUG LABEL: Chest Rub
NDC: 42507-248 | Form: JELLY
Manufacturer: Hy-Vee, Inc.
Category: otc | Type: HUMAN OTC DRUG LABEL
Date: 20260204

ACTIVE INGREDIENTS: MENTHOL 26 mg/1 g; CAMPHOR (NATURAL) 48 mg/1 g; EUCALYPTUS OIL 12 mg/1 g
INACTIVE INGREDIENTS: NUTMEG OIL; PETROLATUM; THYMOL; CEDAR LEAF OIL; TURPENTINE OIL

Hy-Vee 248.001/248AI
Medicated Chest Rub

Disclaimer

Failure to follow these warnings could result in serious consequences

Active ingredients

Camphor 4.8%

Eucalyptus oil 1.2%

Menthol 2.6%

Purpose

cough suppressant & topical analgesic

Uses

- on chest and throat, temporarily relieves cough due to the common cold
- on muscles and joints, temporarily relieves minor aches and pains

Warnings

For external use only; avoid contact with eyes.

Do not use

- by mouth
- with tight bandages
- in nostrils
- on wounds or damaged skin

Ask a doctor before use if you have

- cough that occurs with too much phlegm (mucus)
- persistent or chronic cough such as occurs with smoking, asthma, or emphysema

When using this product, do not

- heat
- microwave
- add to hot water or any container where heating water.

May cause splattering and result in burns.

Stop use and ask a doctor if

- muscle aches and pains persist more than 7 days or come back
- cough lasts more than 7 days, comes back, or occurs with fever, rash or persistent headache.

These could be signs of a serious condition.

If pregnant or breast-feeding,

ask a health professional before use.

Keep out of reach of children.

In case of accidental ingestion, get medical help or contact a Poison Control Center right away.

Directions

See imporatant warnings under "When using this product"

- adults & children 2 yrs & over:
- rub a thick layer on chest and throat or rub on sore aching muscles
- cover with warm, dry cloth if desired
- keep clothing loose about throat/chest to help vapors reach the nose/mouth
- repeat up to three times per 24 hours or as directed by doctor
- children under 2 years of age: ask a doctor

Other information

- store at room temperature

Inactive ingredients

cedarleaf oil, nutmeg oil, special petrolatum, spirits of turpentine, thymol

Disclaimer

*This product is not manufactured or distributed by Procter & Gamble, distributor of VICKS® VAPORUB®.

Claims

The active ingredients in HyVee® Medicated Chest Rub work when you inhale in the medicated vapors to relieve coughing due to colds.

HyVee® Medicated Chest Rub also relieves minor muscle aches and pains.

Adverse Reaction

DISTRIBUTED BY HY-VEE, INC.

5820 WESTOWN PARKWAY

WEST DES MOINES, IA 50266 VIJA1025

Scan here for more information.

SATISFACTION GUARANTEED OR PURCHASE PRICE REFUNDED, FOR INFORMATION CALL 1-800-289-8343

www.hy-vee.com

Principal Display Panel

Hy-Vee®

*Compare to Vicks® VapoRub®

Medicated Chest Rub

COUGH SUPPRESSANT

TOPICAL ANALGESIC

Cough Relief

Soothing Ointment

NET WT 3.53 OZ (100 g)